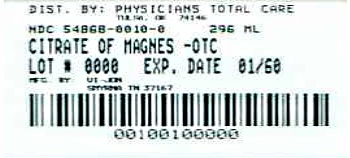 DRUG LABEL: Citrate of Magnesium
NDC: 54868-0010 | Form: LIQUID
Manufacturer: Physicians Total Care, Inc.
Category: otc | Type: HUMAN OTC DRUG LABEL
Date: 20120706

ACTIVE INGREDIENTS: Magnesium citrate 1.745 g/29.6 mL
INACTIVE INGREDIENTS: LEMON OIL; POTASSIUM BICARBONATE; SACCHARIN SODIUM DIHYDRATE; WATER

Drug Facts

Active ingredient
Magnesium citrate 1.745 g per fl oz

Purpose
Saline laxative

INDICATIONS AND USAGE

Use for relief of occasional constipation (irregularity). Generally produces bowel movement in 1/2 to 6 hours

Warnings

Ask a doctor before you use if you have
• kidney disease
• a magnesium or potassium-restricted diet
• abdominal pain, nausea, or vomiting
• noticed a sudden change in bowel habits that persists over a period of 2 weeks
• already used a laxative for a period longer than 1 week

Ask a doctor or pharmacist before use if your are taking any other drug.
Take this product 2 or more hours before or after other drugs. Laxatives may affect how other drugs work.

Stop use and ask a doctor if you have rectal bleeding or failure to have a bowel movement after use.
These could be signs of a serious condition.

PREGNANCY OR BREAST FEEDING

If pregnant or breast-feeding, ask a health professional before use

Keep out of reach of children. In case of overdose, get medical help or contact a Poison Control Center right away.

DOSAGE AND ADMINISTRATION

Directions • drink a full glass (8 ounces) of liquid wit each dose
•may be taken as a single daily dose or in divided doses
adults and children 12 years of age and over -6.5 to 10 fl oz maximum 10 fl oz in 24 hours
children 6 to under 12 years of age - 3 to 7 fl oz maximum 7 fl oz in 24 hours
children 2 to under 6 years of age - ask a doctor
discard unused product within 24 hours of opening bottle

Other information
• magnesium content 290 mg per 1 fl oz (30 mL)
• potassium content 80 mg per 1 fl oz (30 mL)
• store at temperatures between 46⁰ and 86⁰F (8⁰ and 30⁰ C)

Inactive ingredients citric acid, lemon oil, potassium bicarbonate,
sodium saccharin, water purified

ADVERSE REACTIONS

Distributed by:
Vi-Jon
One Swan Drive
Smyrna, TN 37167

Additional barcode labeling by:
Physicians Total Care, Inc.
Tulsa, Oklahoma 74146

PACKAGE LABEL

NDC 54868-0010-0
Very Low Sodium
Citroma
MAGNESIUM CITRATE
Lemony
•Saline Laxative
•Oral Solution
Do not use if tamper evident twist-off cap
is missing, broken or separated from neck ring
10FL OZ (296 mL)